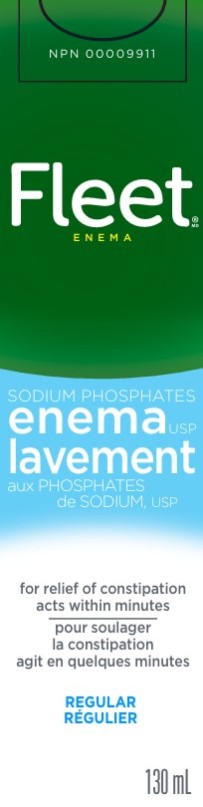 DRUG LABEL: Fleet
NDC: 0132-0560 | Form: ENEMA
Manufacturer: C.B. Fleet Company, Inc.
Category: otc | Type: HUMAN OTC DRUG LABEL
Date: 20251211

ACTIVE INGREDIENTS: SODIUM PHOSPHATE, DIBASIC, HEPTAHYDRATE 6 g/100 mL; SODIUM PHOSPHATE, MONOBASIC 16 g/100 mL
INACTIVE INGREDIENTS: WATER; EDETATE DISODIUM; BENZALKONIUM CHLORIDE

Fleet Enema Adult Canada 0132-0560-40

Active Ingredient (in each 100-mL delivered dose)

Monobasic Sodium Phosphate 16 g................

Dibasic Sodium Phosphate 6 g........................

Purpose

Laxative / Bowel Cleanser

Laxative / Bowel Cleanser

Use

For relief of occasional constipation or bowel cleansing before rectal examinations.

Warnings

Using more than one enema in 24 hours can be harmful.

Ask a doctor before using this product if you

- are on a sodium-restricted diet
- have kidney disease are pregnant or nursing a baby

Ask a doctor before using any laxative if you:

- have abdominal pain, nausea, or vomiting
- have a sudden change in bowel habits lasting more than 2 weeks
- have already used a laxative for more than 1 week

Stop using this product and consult a doctor if you

- have rectal bleeding
- have no bowel movement after the enema is given

These symptoms may indicate a serious condition.

Keep out of reach of children

In case of overdose or accidental ingestion, get medical help right away.

Directions

Single Daily Dosage: Do not use more unless directed by a doctor. See Warnings.
Adults and children 12 years and older: | 120 mL as a single dose
Children 2 to 12 years: | 60 mL as a single dose
Children under 2 years: | Consult a doctor

Other Information

Sodium Content 4.4 g

Inactive Ingredients

benzalkonium chloride, disodium EDTA, purified water

Questions?

C.B. Fleet Co., Inc.

Lynchburg, VA 24502

U.S.A.

PRINCIPAL DISPLAY PANEL

Fleet
SODIUM PHOSPHATES
ENEMA USP
FOR RELIEF OF CONSTIPATION
ACTS WITHIN MINUTES
REGULAR
130 ml